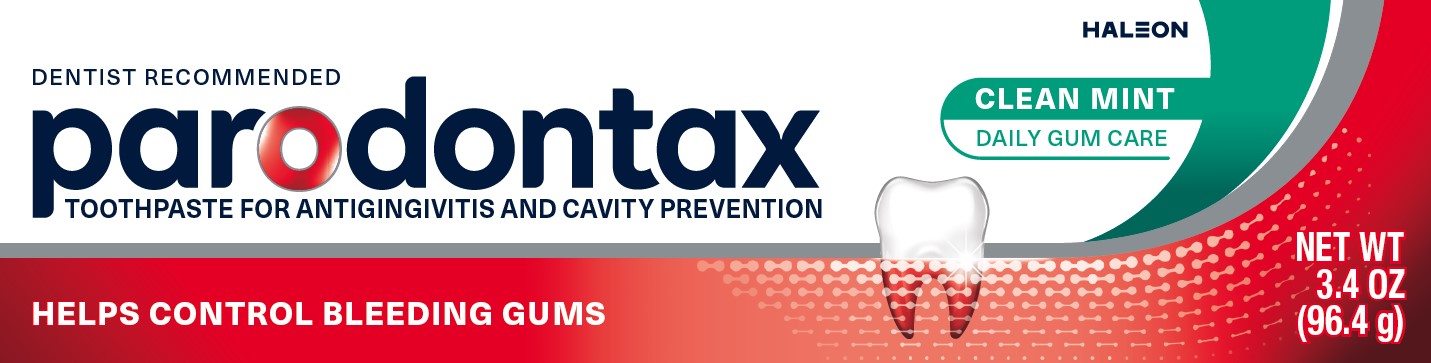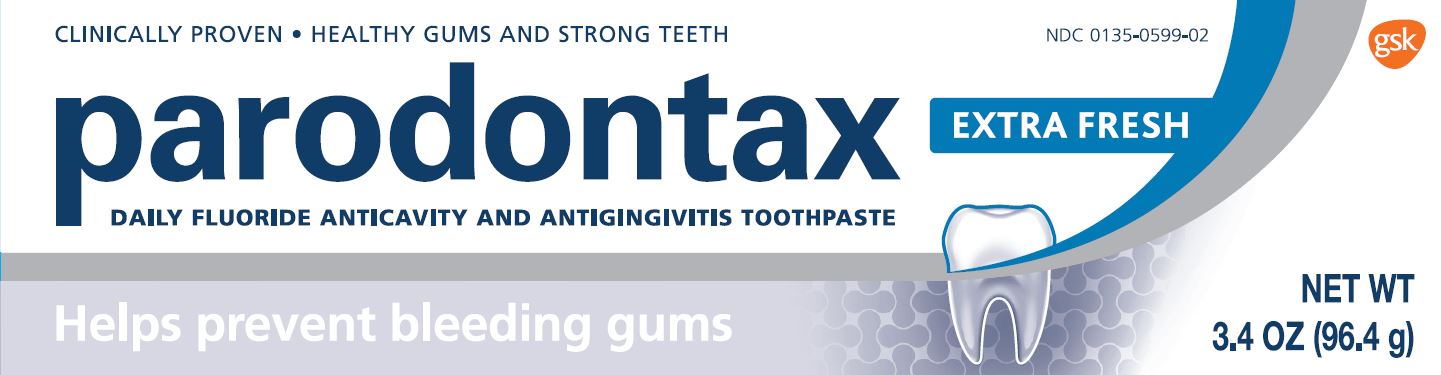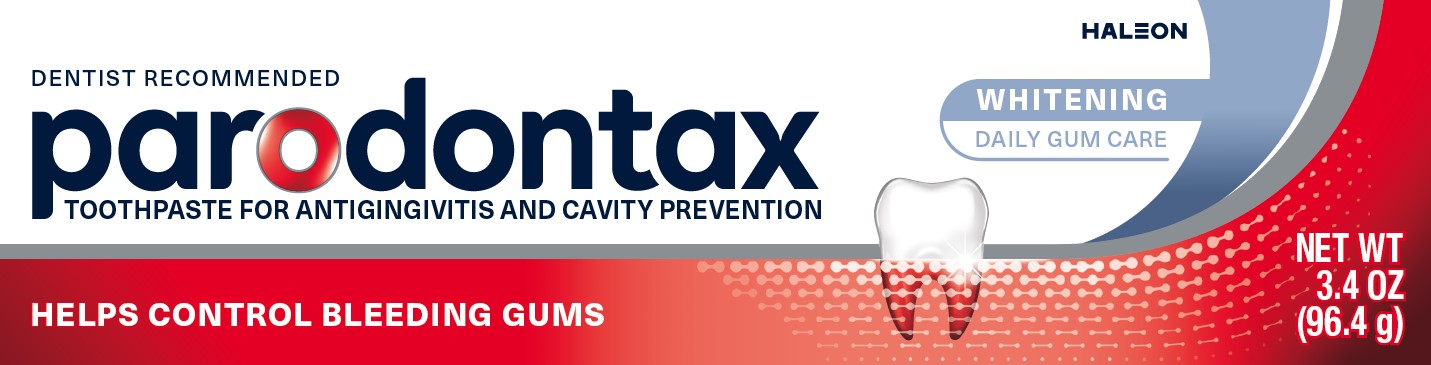 DRUG LABEL: parodontax
NDC: 0135-0598 | Form: PASTE
Manufacturer: Haleon US Holdings LLC
Category: otc | Type: HUMAN OTC DRUG LABEL
Date: 20251222

ACTIVE INGREDIENTS: STANNOUS FLUORIDE 1.10 mg/1 g
INACTIVE INGREDIENTS: GLYCERIN; POLYETHYLENE GLYCOL 400; HYDRATED SILICA; SODIUM TRIPOLYPHOSPHATE ANHYDROUS; SODIUM LAURYL SULFATE; TITANIUM DIOXIDE; CARBOMER HOMOPOLYMER TYPE B (ALLYL PENTAERYTHRITOL CROSSLINKED); COCAMIDOPROPYL BETAINE; SACCHARIN SODIUM

Drug Facts

Active ingredient

Stannous fluoride 0.454 % (0.15 % w/v fluoride ion)

Purposes

Anticavity

Antigingivitis

Uses

- aids in the prevention of dental cavities.
- helps control bleeding gums.
- helps interfere with harmful effects of plaque associated with gingivitis.

Warnings

Stop use and ask a dentist if

- gingivitis, bleeding, or redness persists for more than 2 weeks.
- you have painful or swollen gums, pus from the gum line, loose teeth, or increasing spacing between the teeth. These may be signs or symptoms of periodontitis, a serious form of gum disease.

Keep out of reach of children under 6 years of age.

If more than used for brushing is accidentally swallowed, get medical help or contact a Poison Control Center right away.

Directions

- adults and children 2 years of age and older:
  - brush teeth thoroughly, preferably after each meal at least twice a day, or as directed by a dentist or doctor. Minimize swallowing.
  - to minimize swallowing for children under 6 years of age, use a pea-sized amount and supervise brushing and rinsing until good habits are established.
- children under 2 years of age: Consult a dentist or doctor.

Other information

- products containing stannous fluoride may produce surface staining of the teeth. Adequate toothbrushing may prevent these stains which are not harmful or permanent and may be removed by your dentist.
- this product is specially formulated to help prevent staining.
- do not store above 25ºC (77ºF)

Inactive ingredients

glycerin, PEG-8, hydrated silica, pentasodium triphosphate, flavor, sodium lauryl sulfate, titanium dioxide, polyacrylic acid, cocamidopropyl betaine, sodium saccharin

Questions or comments?

Call toll-free 1-866-844-2797

Additional Information

ALWAYS FOLLOW THE LABEL

Healthy gums don’t bleed

If you spit blood when you brush or floss, it could be a sign of early gum disease. parodontax is clinically proven to help reduce bleeding gums* by removing the plaque buildup that can cause gums to swell and bleed.

parodontax is a daily fluoride toothpaste that also prevents cavities, provides fresh breath, and whitens – for healthy gums and strong teeth.

parodontax toothpaste offers a fresh, minty flavor.

*with twice daily brushing

Unhealthy gums

Healthy gums

ADA Accepted
American Dental Association ®

Principal Display Panel - Clean Mint

DENTIST RECOMMENDED

parodontax

TOOTHPASTE FOR ANTIGINGIVITIS AND CAVITY PREVENTION

CLEAN MINT

DAILY GUM CARE

HELPS CONTROL BLEEDING GUMS

NET WT 3.4 OZ (96.4 g)

Principal Display Panel – Extra Fresh

CLINICALLY PROVEN ∙ HEALTHY GUMS AND STRONG TEETH

NDC 0135-0599-02

parodontax

EXTRA FRESH

DAILY FLUORIDE ANTICAVITY AND ANTIGINGIVITIS TOOTHPASTE

Helps prevent bleeding gums

NET WT

3.4 OZ (96.4 g)

PLAQUE BUILDS UP

GUMS SWELL AND BLEED

PARODONTAX HELPS REMOVE PLAQUE

Healthy gums don’t bleed

If you spit blood when you brush or floss it could be a sign of early gum disease. parodontax is clinically proven to help reduce bleeding gums by removing the plaque buildup that can cause gums to swell and bleed.

parodontax is a daily fluoride toothpaste that also prevents cavities, provides fresh breath and whitening- for healthy gums and strong teeth.

Principal Display Panel – Whitening

DENTIST RECOMMENDED

parodontax

TOOTHPASTE FOR ANTIGINGIVITIS AND CAVITY PREVENTION

WHITENING

DAILY GUM CARE

HELPS CONTROL BLEEDING GUMS

NET WT 3.4 OZ (96.4 g)